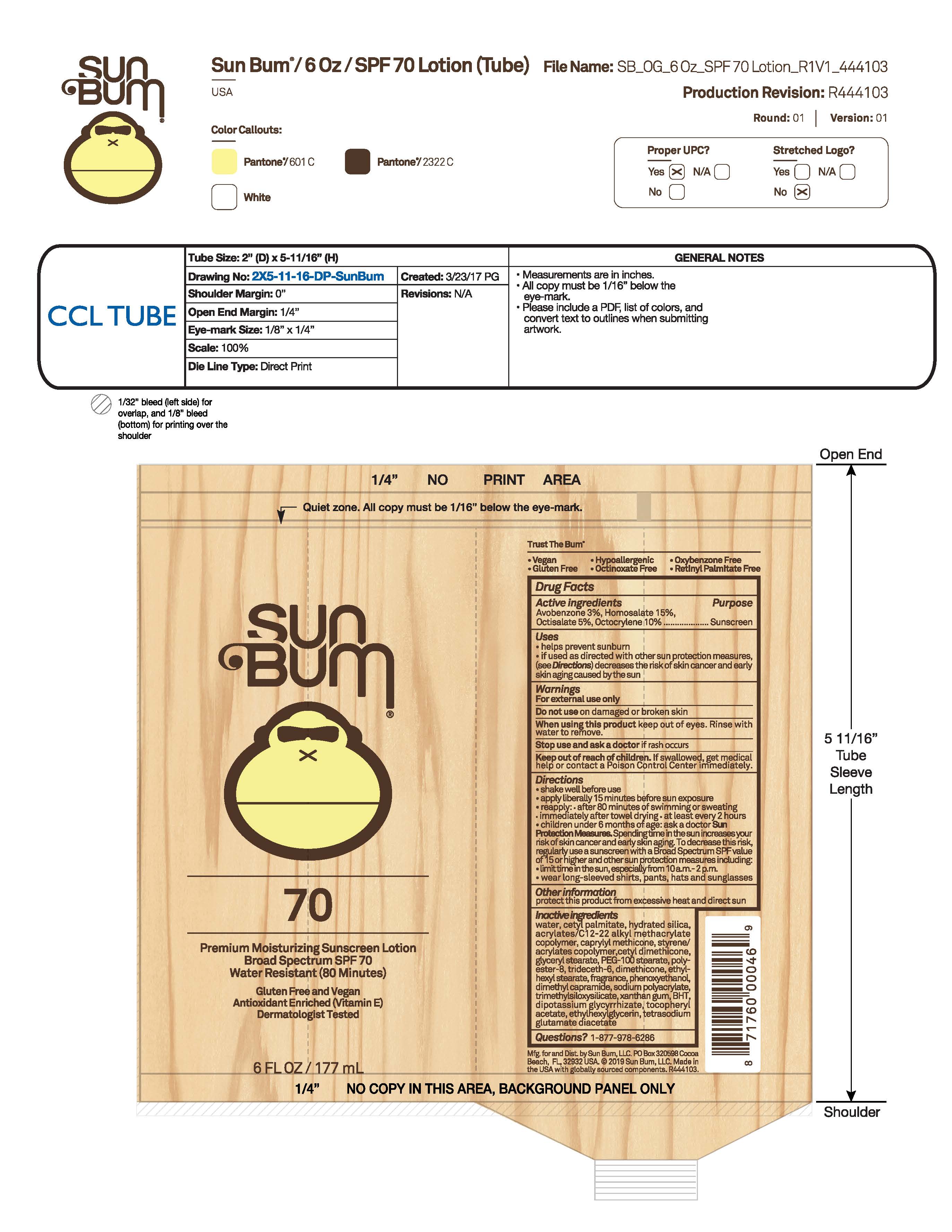 DRUG LABEL: Sun Bum 70 Premium Sunscreen
NDC: 69039-750 | Form: LOTION
Manufacturer: Sun Bum, LLC
Category: otc | Type: HUMAN OTC DRUG LABEL
Date: 20250818

ACTIVE INGREDIENTS: OCTOCRYLENE 100 mg/1 mL; AVOBENZONE 30 mg/1 mL; OCTISALATE 50 mg/1 mL; HOMOSALATE 150 mg/1 mL
INACTIVE INGREDIENTS: DIMETHICONE; PEG-100 STEARATE; TRIMETHYLSILOXYSILICATE (M/Q 0.6-0.8); CETYL DIMETHICONE 25; ETHYLHEXYL STEARATE; ACRYLATES/C10-30 ALKYL ACRYLATE CROSSPOLYMER (60000 MPA.S); BHT; .ALPHA.-TOCOPHEROL ACETATE; DIPOTASSIUM GLYCYRRHIZATE; TETRASODIUM GLUTAMATE DIACETATE; WATER; HYDRATED SILICA; PHENOXYETHANOL; GLYCERYL STEARATE; DIMETHYL CAPRAMIDE; SODIUM POLYACRYLATE (8000 MW); XANTHAN GUM; ETHYLHEXYLGLYCERIN; CETYL PALMITATE; CAPRYLYL METHICONE; LUVISET 360; POLYESTER-8 (1400 MW, CYANODIPHENYLPROPENOYL CAPPED); TRIDECETH-6

Sun Bum 70 Premium Sunscreen

Active Ingredients

AVOBENZONE 3%, HOMOSALATE 15%, OCTISALATE 5%, OCTOCRYLENE 10%

Purpose

Sunscreen

Uses

• helps prevent sunburn • if used as directed with other sun protection measures, (see Directions) decreases the risk of skin cancer and early skin aging caused by the sun

Warnings

For external use only

Do not use on damaged or broken skin

When using this product keep out of eyes. Rinse with water to remove.

Stop use and ask a doctor if rash occurs

Keep out of reach of children. If swallowed, get medical help or contact a Poison Control Center immediately.

Warnings

Keep Out Of Reach Of Children

Directions

• shake well before use

• apply liberally 15 minutes before sun exposure

• reapply: • after 80 minutes of swimming or sweating • immediately after towel drying • at least every 2 hours

• children under 6 months of age: ask a doctor

• Sun Protection Measures. Spending time in the sun increases your risk of skin cancer and early skin aging. To decrease this risk, regularly use a sunscreen with a Broad Spectrum SPF value of 15 or higher and other sun protection measures including:

• limit time in the sun, especially from 10 a.m.- 2 p.m.

• wear long-sleeved shirts, pants, hats and sunglasses

Directions

• shake well before use

• apply liberally 15 minutes before sun exposure

Other Information

protect this product from excessive heat and direct sun

Inactive Ingredients

WATER, CETYL PALMITATE, HYDRATED SILICA, ACRYLATES/C12-22 ALKYL ACRYLATE CROSSPOLYMER, CAPRYLYL METHICONE, STYRENE/ACRYLATES COPOLYMER, CETYL DIMETHICONE, GLYCERYL STEARATE, PEG-100 STEARATE, POLYESTER-8, TRIDECETH-6, DIMETHICONE, ETHYLHEXYL STEARATE, FRAGRANCE, PHENOXYETHANOL, DIMETHYL CAPRAMIDE, SODIUM POLYACRYLATE, TRIMETHYLSILOXYSILICATE, XANTHAN GUM, BHT, DIPOTASSIUM GLYCYRRHIZATE, TOCOPHEROL ACETATE, ETHYLHEXYLGLYCERIN, TETRASODIUM GLUTAMATE DIACETATE

Questions?

1-877-978-6286